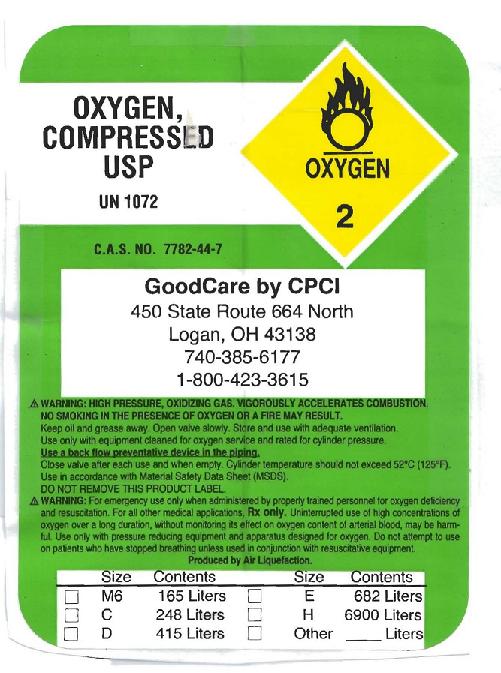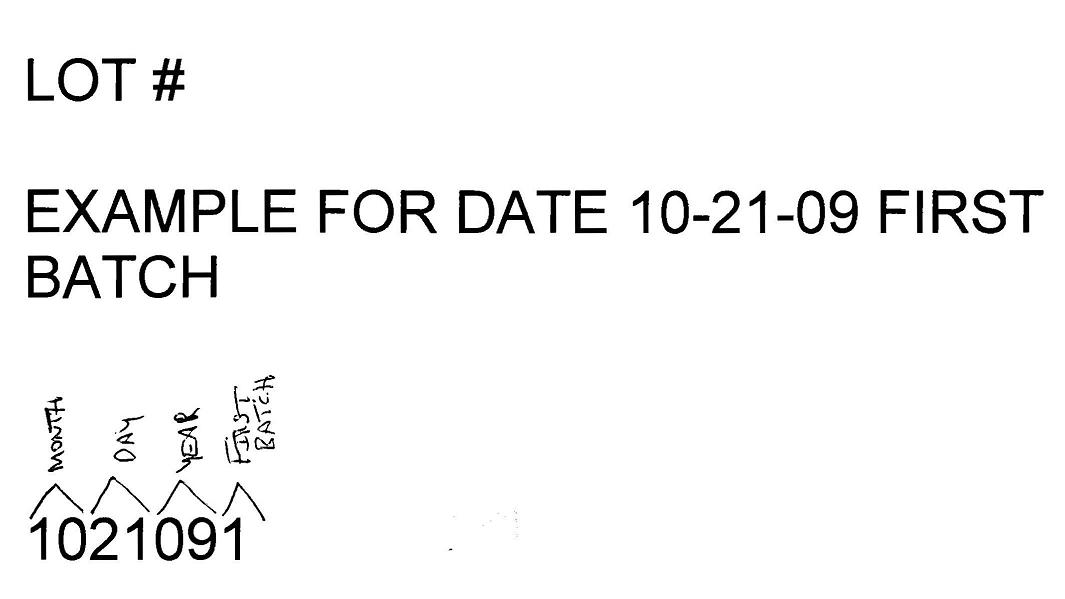 DRUG LABEL: Oxygen
NDC: 53748-0001 | Form: GAS
Manufacturer: GoodCare by CPCI
Category: prescription | Type: HUMAN PRESCRIPTION DRUG LABEL
Date: 20091030

ACTIVE INGREDIENTS: Oxygen 99 L/100 L

Oxygen